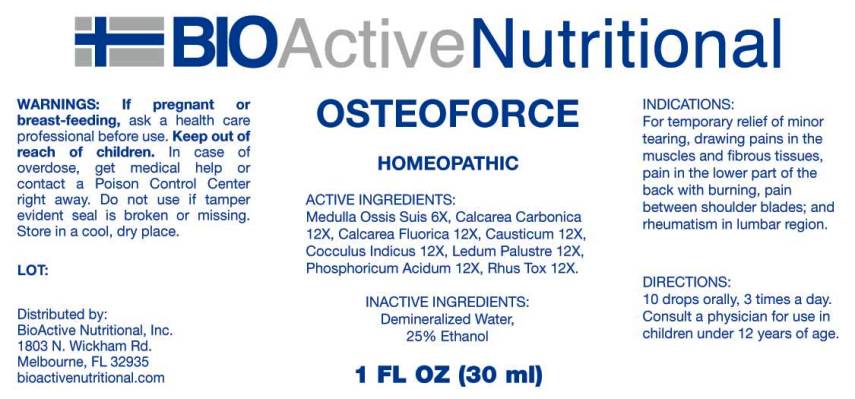 DRUG LABEL: Osteoforce
NDC: 43857-0351 | Form: LIQUID
Manufacturer: BioActive Nutritional, Inc.
Category: homeopathic | Type: HUMAN OTC DRUG LABEL
Date: 20250401

ACTIVE INGREDIENTS: SUS SCROFA BONE MARROW 6 [hp_X]/1 mL; OYSTER SHELL CALCIUM CARBONATE, CRUDE 12 [hp_X]/1 mL; CALCIUM FLUORIDE 12 [hp_X]/1 mL; CAUSTICUM 12 [hp_X]/1 mL; ANAMIRTA COCCULUS SEED 12 [hp_X]/1 mL; RHODODENDRON TOMENTOSUM LEAFY TWIG 12 [hp_X]/1 mL; PHOSPHORIC ACID 12 [hp_X]/1 mL; TOXICODENDRON PUBESCENS LEAF 12 [hp_X]/1 mL
INACTIVE INGREDIENTS: WATER; ALCOHOL

DRUG FACTS:

ACTIVE INGREDIENTS:

Calcarea Carbonica 12X, Calcarea Fluorica 12X, Causticum 12X, Cocculus Indicus 12X, Ledum Palustre 12X, Medulla Ossis Suis 6X, Phosphoricum Acidum 12X, Rhus Tox 12X.

PURPOSE:

Calcarea Carbonica - cramps,** Calcarea Fluorica – joint pain,** Causticum - inflammation,** Cocculus Indicus - dizziness,** Ledum Palustre - swelling,** Medulla Ossis Suis – arthritic pain,** Phosphoricum Acidum - weakness,** Rhus Tox – joint pain**

**Claims based on traditional homeopathic practice, not accepted medical evidence. Not FDA evaluated.

USES:

For temporary relief of minor tearing, drawing pains in the muscles and fibrous tissues, pain in the lower part of the back with burning, pain between shoulder blades; and rheumatism in lumbar region.

WARNINGS:

If pregnant or breast-feeding, ask a health care professional before use.

Keep out of reach of children. In case of overdose, get medical help or contact a Poison Control Center right away.

Do not use if tamper evident seal is broken or missing.

Store in a cool, dry place.

KEEP OUT OF REACH OF CHILDREN:

In case of overdose, get medical help or contact a Poison Control Center right away.

DIRECTIONS:

• 10 drops orally, 3 times a day.

• Consult a health care professional for use in children under 12 years of age.

INACTIVE INGREDIENTS:

Demineralized Water, 25% Ethanol

QUESTIONS:

Distributed by:
BioActive Nutritional, Inc.
1803 N. Wickham Rd.
Melbourne, FL 32935
bioactivenutritional.com

1-800-288-9525

PACKAGE LABEL DISPLAY:

BIOActive Nutritional

OSTEOFORCE

HOMEOPATHIC

1 FL OZ (30 ml)